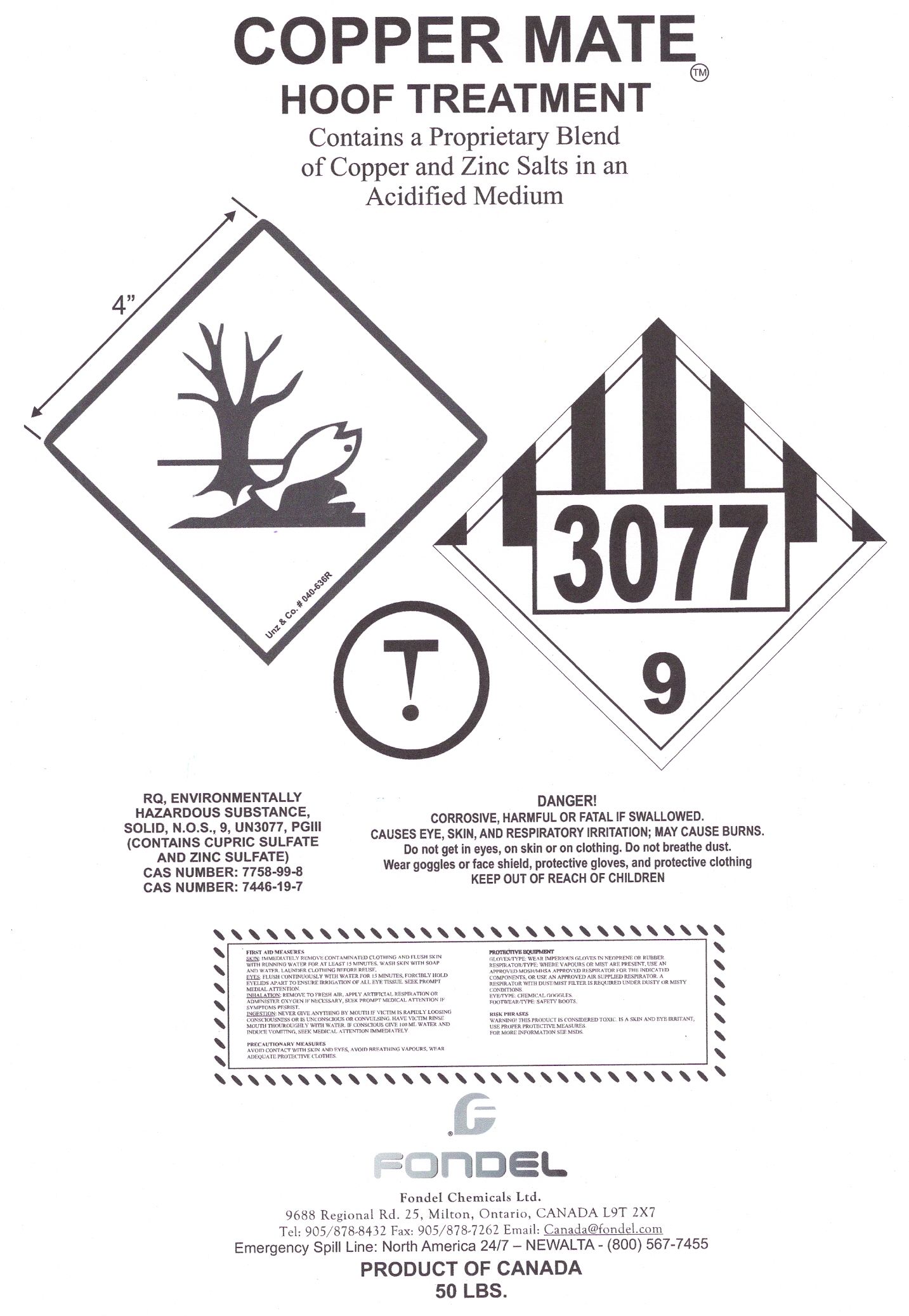 DRUG LABEL: Copper Mate
NDC: 51044-401 | Form: POWDER, FOR SOLUTION
Manufacturer: Fondel Chemical Ltd.
Category: animal | Type: OTC ANIMAL DRUG LABEL
Date: 20101203

ACTIVE INGREDIENTS: Cupric Sulfate 0.25 kg/1.6 kg; ZINC SULFATE MONOHYDRATE 0.1 kg/1.6 kg; CITRIC ACID MONOHYDRATE 0.05 kg/1.6 kg

Copper Mate Drug Facts Label

Active Ingredients: Cupric Sulfate, Zinc Sulfate, Citric Acid [Powder for use in solution]

ASK DOCTOR

Directions: It is recommended for use in a 1% to 3% solution strength (by weight) with immersion lasting between 5 and 20 minutes, once or twice daily, for a period of time as prescribed by your veterinarian.

Warnings:

- Copper and Zinc can be toxic to sheep. Do not allow animals to eat or drink the Copper Mate powder or hoof bath solution.
- Know the volume of the hoof bath and calculate the amount of Copper Mate carefully.
- DO NOT OVER DOSE by using more Copper Mate than what is recommended by your veterinarian.

For External Use Only

Keep out of reach of children.

PURPOSE

Purpose: Copper Mate powder is used as an aid in hoof rot management under veterinary guidance.

Use: Copper Mate powder is used in hoof baths for cattle and sheep.

When Using this Product: By placing a clean water bath ahead of the treatment bath, animals will clean their hooves to some extent and keep the treatment bath clean longer. Hoof baths should only be part of an overall program that includes proper nutrition, regular hoof trimming, and hoof injury prevention.

QUESTIONS

Questions?: 1-800-567-7455 (24/7-Emergency Spill Line) or 1-905-878-8432

Copper Mate Bag Label

COPPER MATE
HOOF TREATMENT
Contains a Proprietary Blend of Copper and Zinc Salts in an Acidified Medium
FIRST AID MEASURES
SKIN: IMMEDIATELY REMOVE CONTAMINATED CLOTHING AND FLUSH SKIN WITH RUNNING WATER FOR AT LEAST 15 MINUTES. WASH SKIN WITH SOAP AND WATER. LAUNDER CLOTHING BEFORE REUSE.
EYES: FLUSH CONTINUOUSLY WITH WATER FOR 15 MINUTES. FORCIBLY HOLD EYELIDS APART TO ENSURE IRRIGATION OF ALL EYE TISSUE. SEEK PROMPT MEDICAL ATTENTION.
INHALATION: REMOVE TO FRESH AIR. APPLY ARTIFICIAL RESPIRATION OR ADMINISTER OXYGEN IF NECESSARY. SEEK PROMPT MEDICAL ATTENTION IF SYMPTOMS PERSIST.
INGESTION: NEVER GIVE ANYTHING BY MOUTH IF VICTIM IS RAPIDLY LOSING CONSCIOUSNESS OR IS UNCONCIOUS OR CONVULSING. HAVE VICTIM RINSE MOUTH THROUGHLY WITH WATER. IF CONSIOUS GIVE 100 ML OF WATER AND INDUCE VOMITING. SEEK MEDICAL ATTENTION IMMEDIATELY.
PRECAUTIONARY MEASURES
AVOID CONTACT WITH SKIN AND EYES. AVOID BREATHING VAPOURS.
WEAR ADEQUATE PROTECTIVE CLOTHES
PRECAUTIONARY EQUIPMENT
GLOVES/TYPE: WEAR IMPERVIOUS GLOVES IN NEOPRENE OR RUBBER.
RESPIRATOR TYPE: WHERE VAPOURS OR MIST ARE PRESENT, USE AN APPROVED NIOSH/MHSA APPROVED RESPIRATOR FOR THE INDICATED COMPONENTS, OR USE AN APPROVED AIR SUPPLIED RESPIRATOR. A RESPIRATOR WITH DUST/MIST FILTER IS REQUIRED UNDER DUSTY OR MISTY CONDITIONS.
EYE/TYPE: CHEMICAL GOOGLES.
FOOTWEAR/TYPE: SAFETY BOOTS.
RISK PHRASES
WARNING! THIS PRODUCT IS CONSIDERED TOXIC. IS A SKIN AND EYE IRRITANT. USE PROPER PROTECTIVE MEASURES. FOR MORE INFORMATION SEE MSDS.
FONDEL Chemicals Ltd.
9688 Regional Rd. 25, Milton, Ontario, CANADA L9T 2X7
Tel: 905/878-8432 Fax: 905/878-7262 E-mail: Canada@fondel.com
Emergency Spill Line: North America 24/7 – NEWALTA- (800) 567-7455
PRODUCT OF CANADA
50 LBS. 25 KG.